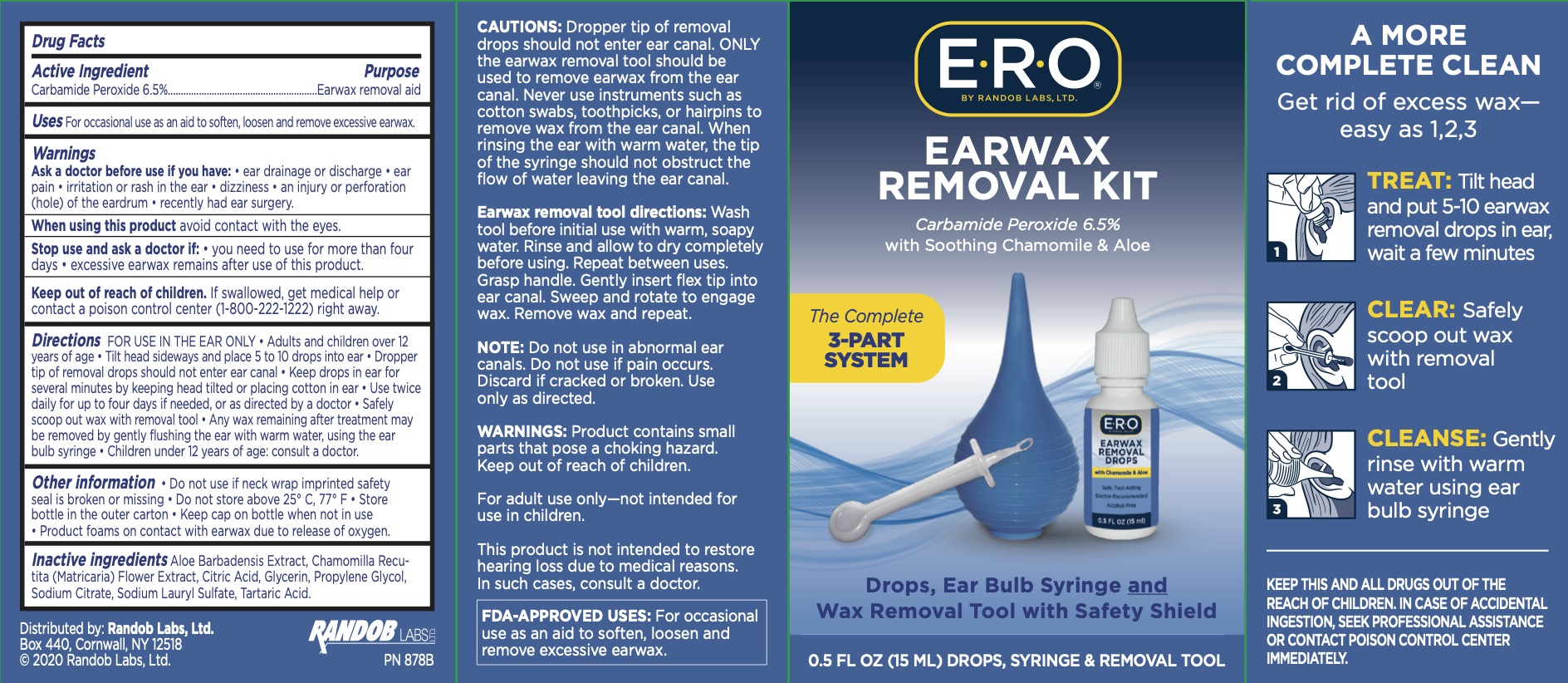 DRUG LABEL: ERO Ear Wax Removal Kit
NDC: 52412-175 | Form: LIQUID
Manufacturer: Randob Labs
Category: otc | Type: HUMAN OTC DRUG LABEL
Date: 20241215

ACTIVE INGREDIENTS: CARBAMIDE PEROXIDE 6.5 g/100 mL
INACTIVE INGREDIENTS: CHAMOMILE; CITRIC ACID MONOHYDRATE; PROPYLENE GLYCOL; TARTARIC ACID; SODIUM LAURYL SULFATE; SODIUM CITRATE; GLYCERIN; ALOE VERA LEAF

ERO Ear Wax Removal Kit

ACTIVE INGREDIENT

Carbamide Peroxide 6.5%

PURPOSE

Earwax removal aid

INDICATIONS AND USAGE

For occasional use as an aid to soften, loosen, and remove excessive earwax.

Ask a doctor before use if you have

- if you have ear drainage or discharge, ear pain, irritation or rash in the ear, dizziness
- an injury or perforation (hole) of the eardrum, recently had ear surgery

When using this product avoid contact with the eyes

Stop use and ask a doctor if you need to use for more than four days, excessive earwax remains after use of this product.

KEEP OUT OF REACH OF CHILDREN

If product is swallowed, get medical help or contact a Poison Control Center right away.

DOSAGE AND ADMINISTRATION

FOR IN EAR USE ONLY. Adults and children over 12 years of age: tilt head sideways and place 5 to 10 drops into ear. Tip of applicator should not enter ear canal. Keep drops in ear for several minutes by keeping head tilted or placing cotton in the ear. Use twice daily for up to 4 days if needed, or as directed by a doctor.

Any wax remaining after treatment may be removed by gently flushing the ear with warm water, using a soft rubber bulb ear syringe. Children under 12 years of age: consult a doctor.

INACTIVE INGREDIENT

Aloe Barbadensis Extract, Chamomilla Recutita (Matricaria) Flower Extract, Citric Acid, Glycerin, Propylene Glycol, Sodium Citrate, Sodium Lauryl Sulfate, Tartaric Acid.